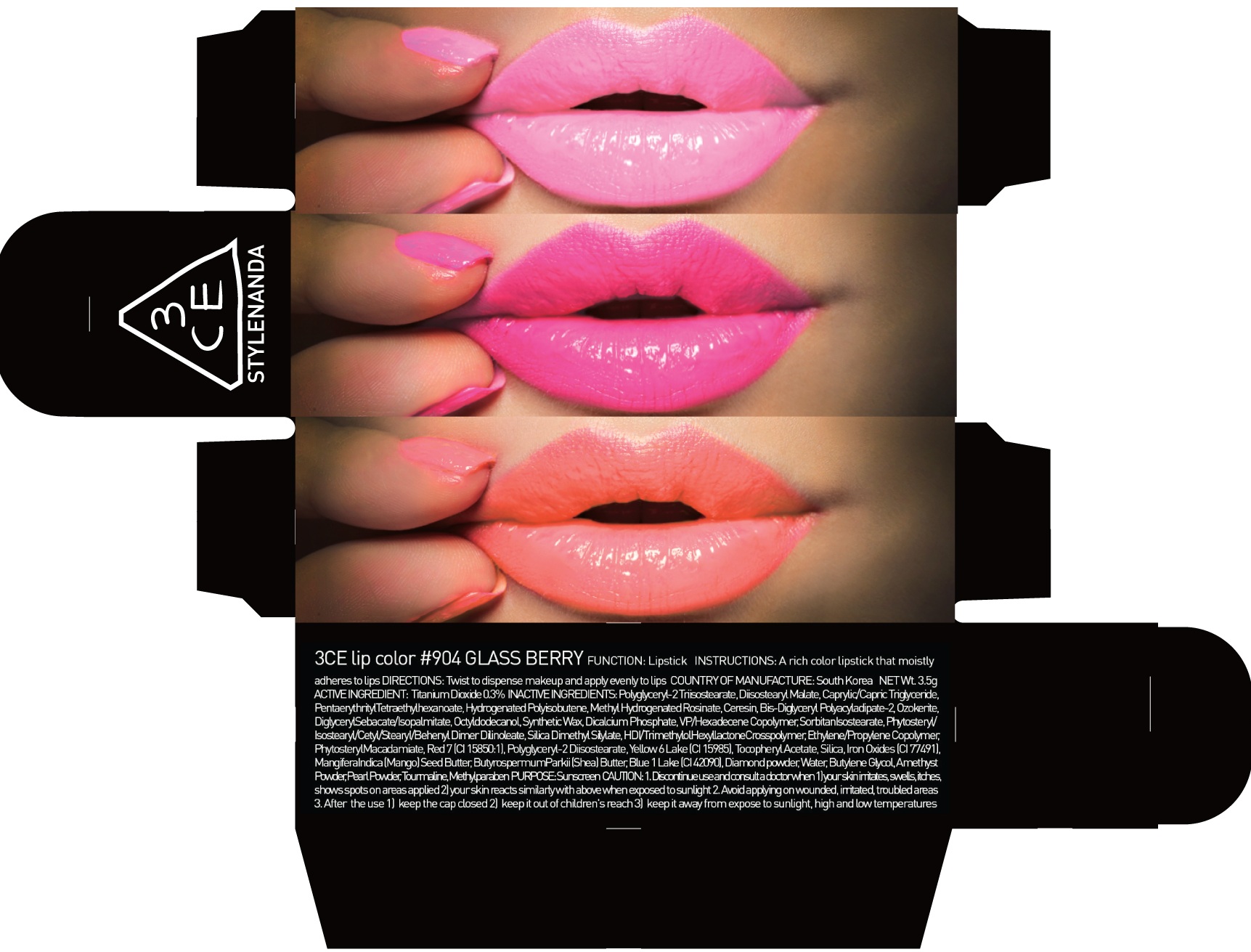 DRUG LABEL: 3CE LIP COLOR 904 GLASS BERRY
NDC: 60764-048 | Form: LIPSTICK
Manufacturer: Nanda Co., Ltd
Category: otc | Type: HUMAN OTC DRUG LABEL
Date: 20160930

ACTIVE INGREDIENTS: Titanium Dioxide 0.010 g/3.5 g
INACTIVE INGREDIENTS: Diisostearyl Malate; Ceresin

ACTIVE INGREDIENT

Active Ingredient: Titanium Dioxide 0.3%

INACTIVE INGREDIENT

Inactive Ingredients: Polyglyceryl-2 Triisostearate, Diisostearyl Malate, Caprylic/Capric Triglyceride, PentaerythritylTetraethylhexanoate, Hydrogenated Polyisobutene, Methyl Hydrogenated Rosinate, Ceresin, Bis-Diglyceryl Polyacyladipate-2, Ozokerite, DiglycerylSebacate/Isopalmitate, Octyldodecanol, Synthetic Wax, Dicalcium Phosphate, VP/Hexadecene Copolymer, SorbitanIsostearate, Phytosteryl/Isostearyl/Cetyl/Stearyl/Behenyl Dimer Dilinoleate, Silica Dimethyl Silylate, HDI/TrimethylolHexyllactoneCrosspolymer, Ethylene/Propylene Copolymer, PhytosterylMacadamiate, Red 7 (CI 15850:1), Polyglyceryl-2 Diisostearate, Yellow 6 Lake (CI 15985), Tocopheryl Acetate, Silica, Iron Oxides (CI 77491), MangiferaIndica (Mango) Seed Butter, ButyrospermumParkii (Shea) Butter, Blue 1 Lake (CI 42090), Diamond powder, Water, Butylene Glycol, Amethyst Powder, Pearl Powder, Tourmaline, Methylparaben

PURPOSE

Purpose: Sunscreen

CAUTION

CAUTION: 1. Discontinue use and consult a doctor when - your skin irritates, swells, itches, shows spots on areas applied - your skin reacts similarly with above when exposed to sunlight 2. Avoid applying on wounded, irritated, troubled areas 3. After the use - keep the cap closed - keep it out of children's reach - keep it away from expose to sunlight, high and low temperatures

DESCRIPTION

INSTRUCTIONS: A rich color lipstick that moistly adheres to lips.

Directions: Twist to dispense makeup and apply evenly to lips